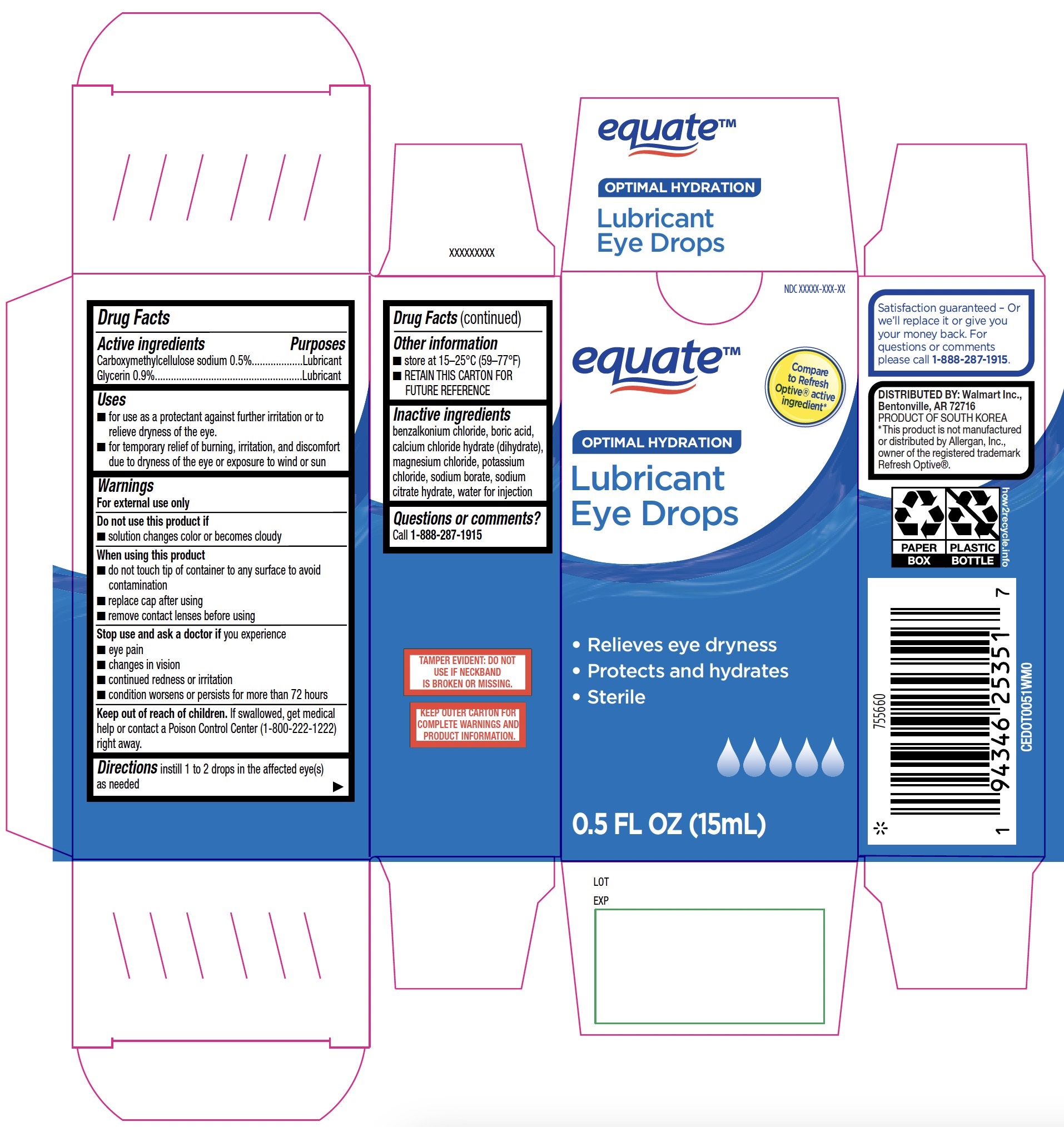 DRUG LABEL: Equate Optimal Hydration Lubricant Eye Drops
NDC: 79903-258 | Form: SOLUTION/ DROPS
Manufacturer: Walmart, Inc.
Category: otc | Type: HUMAN OTC DRUG LABEL
Date: 20251230

ACTIVE INGREDIENTS: CARBOXYMETHYLCELLULOSE SODIUM 0.5 g/100 mL; GLYCERIN 0.9 g/100 mL
INACTIVE INGREDIENTS: MAGNESIUM CHLORIDE; TRISODIUM CITRATE DIHYDRATE; CALCIUM CHLORIDE; SODIUM BORATE; WATER; POTASSIUM CHLORIDE; BENZALKONIUM CHLORIDE; BORIC ACID

Equate Optimal Hydration Lubricant Eye Drops 15mL (PLD)

Active ingredients

Carboxymethylcellulose sodium 0.5%

Glycerin 0.9%

Purposes

Lubricant

Lubricant

Uses

- for use as a protectant against further irritation or to relieve dryness of the eye
- for temporary relief of burning, irritation, and discomfort due to dryness of the eye or exposure to wind or sun

Warnings

For external use only

Do not use this product if

- solution changes color or becomes cloudy

When using this product

- do not touch tip of container to any surface to avoid contamination
- replace cap after using
- remove contact lenses before using

Stop use and ask a doctor if you experience

- eye pain
- changes in vision
- continued redness or irritation
- condition worsens or persists for more than 72 hours

Keep out of reach of children.

If swallowed, get medical help or contact a Poison Control Center (1-800-222-1222) right away.

Directions

instill 1 to 2 drops in the affected eye(s) as needed

Other information

- store at 15-25°C (59-77°F)
  - RETAIN THIS CARTON FOR FUTURE REFERENCE

Inactive ingredients

benzalkonium chloride, boric acid, calcium chloride hydrate (dihydrate), magnesium chloride, potassium chloride, sodium borate, sodium citrate hydrate, water for injection

Questions or comments?

Call 1-888-287-1915